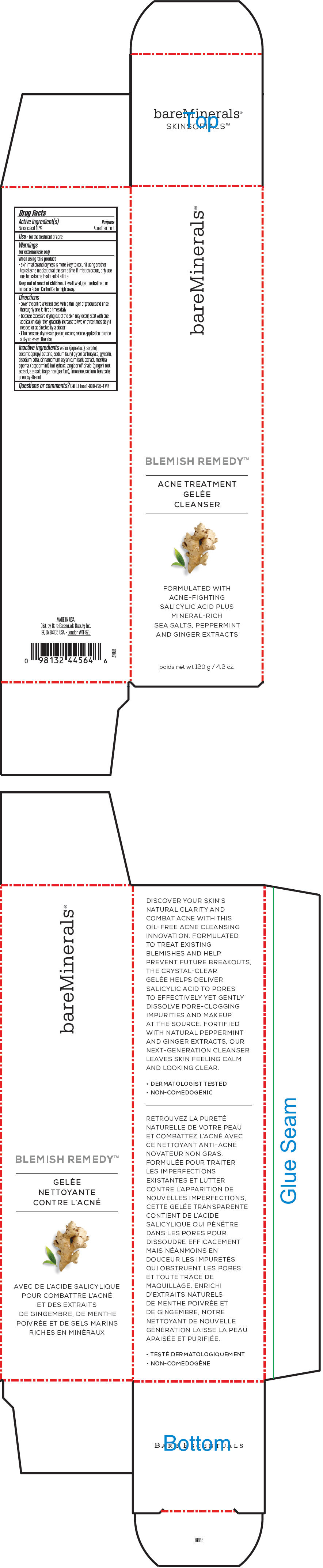 DRUG LABEL: bareMinerals Blemish Remedy Acne Treatment Gelee Cleanser
NDC: 98132-770 | Form: EMULSION
Manufacturer: Orveon Global US LLC
Category: otc | Type: HUMAN OTC DRUG LABEL
Date: 20241022

ACTIVE INGREDIENTS: SALICYLIC ACID 10 mg/1 g
INACTIVE INGREDIENTS: WATER; SORBITOL; COCAMIDOPROPYL BETAINE; SODIUM LAURYL GLYCOL CARBOXYLATE; GLYCERIN; EDETATE DISODIUM; CINNAMON BARK OIL; MENTHA PIPERITA LEAF; GINGER; SEA SALT; LIMONENE, (+/-)-; SODIUM BENZOATE; PHENOXYETHANOL

bareMinerals® Blemish Remedy™ Acne Treatment Gelée Cleanser

Drug Facts

Active ingredient(s)

Salicylic acid 1.0%

Purpose

Acne Treatment

Use

- For the treatment of acne.

Warnings

For external use only

When using this product

- skin irritation and dryness is more likely to occur if using another topical acne medication at the same time. If irritation occurs, only use one topical acne treatment at a time

Keep out of reach of children. If swallowed, get medical help or contact a Poison Control Center right away.

Directions

- cover the entire affected area with a thin layer of product and rinse thoroughly one to three times daily
- because excessive drying out of the skin may occur, start with one application daily, then gradually increase to two or three times daily if needed or as directed by a doctor
- if bothersome dryness or peeling occurs, reduce application to once a day or every other day

Inactive ingredients

water (aqua/eau), sorbitol, cocamidopropyl betaine, sodium lauryl glycol carboxylate, glycerin, disodium edta, cinnamomum zeylanicum bark extract, mentha piperita (peppermint) leaf extract, zingiber officinale (ginger) root extract, sea salt, fragrance (parfum), limonene, sodium benzoate, phenoxyethanol.

Questions or comments?

Call toll free 1-888-795-4747

Dist. by Bare Escentuals Beauty, Inc.
SF, CA 94105 USA

PRINCIPAL DISPLAY PANEL - 120 g Tube Carton

bareMinerals®

BLEMISH REMEDY™

ACNE TREATMENT
GELÉE
CLEANSER

FORMULATED WITH
ACNE-FIGHTING
SALICYLIC ACID PLUS
MINERAL-RICH
SEA SALTS, PEPPERMINT
AND GINGER EXTRACTS

poids net wt 120 g / 4.2 oz.